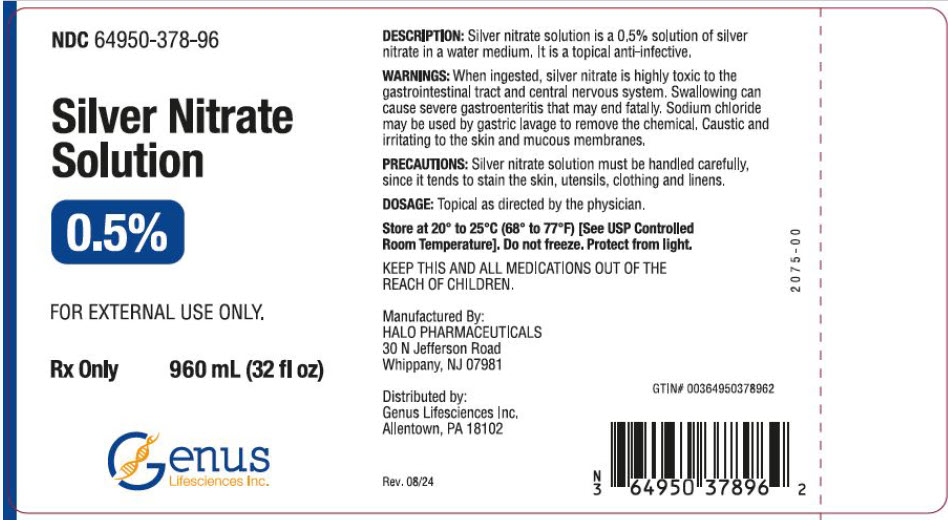 DRUG LABEL: Silver Nitrate
NDC: 64950-378 | Form: SOLUTION
Manufacturer: Genus Lifesciences
Category: prescription | Type: HUMAN PRESCRIPTION DRUG LABEL
Date: 20241030

ACTIVE INGREDIENTS: Silver Nitrate 0.005 g/1 mL
INACTIVE INGREDIENTS: water

Silver Nitrate Solution 0.5%

DESCRIPTION

Silver nitrate solution is a 0.5% solution of silver nitrate in a water medium. It is a topical anti-infective.

WARNINGS

When ingested, silver nitrate is highly toxic to the gastrointestinal tract and central nervous system. Swallowing can cause severe gastroenteritis that may end fatally. Sodium chloride may be used by gastric lavage to remove chemical. Caustic and irritating to the skin and mucous membranes.

PRECAUTIONS

Silver nitrate solution must be handled carefully, since it tends to stain the skin, utensils, clothing and linens.

DOSAGE

Topical as directed by the physician.

KEEP THIS AND ALL MEDICATIONS OUT OF THE REACH OF CHILDREN.

Manufactured By:
HALO PHARMACEUTICALS
30 N Jefferson Road
Whippany, NJ 07981

Distributed by:
Genus Lifesciences Inc.
Allentown, PA 18102

Rev. 08/24

PRINCIPAL DISPLAY PANEL - 960 mL Bottle Label

NDC 64950-378-96

Silver Nitrate
Solution

0.5%

FOR EXTERNAL USE ONLY.

Rx Only
960 mL (32 fl oz)

Genus
Lifesciences Inc.